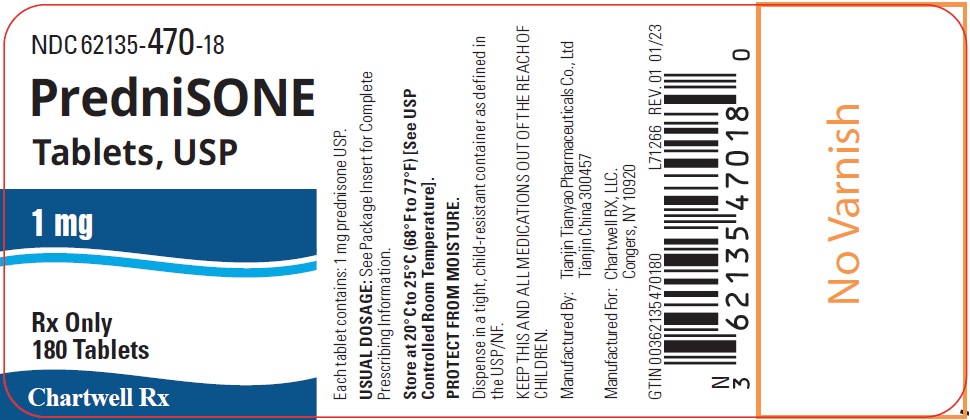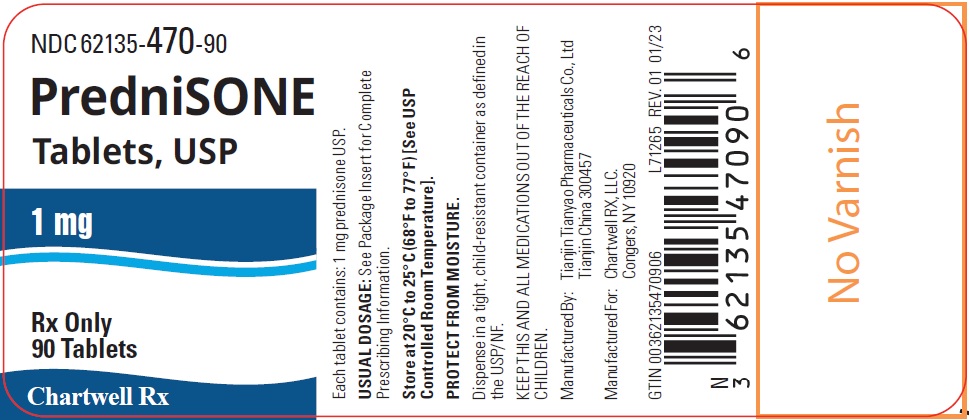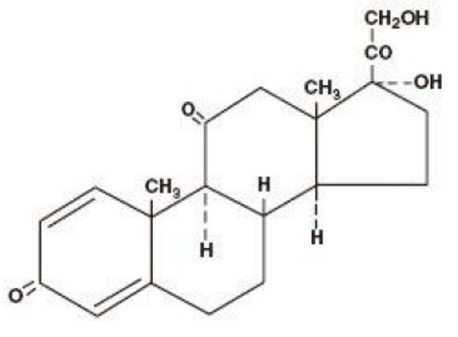 DRUG LABEL: Prednisone
NDC: 62135-470 | Form: TABLET
Manufacturer: Chartwell RX, LLC
Category: prescription | Type: HUMAN PRESCRIPTION DRUG LABEL
Date: 20251211

ACTIVE INGREDIENTS: PREDNISONE 1 mg/1 1
INACTIVE INGREDIENTS: MAGNESIUM STEARATE; LACTOSE MONOHYDRATE; MICROCRYSTALLINE CELLULOSE; SODIUM STARCH GLYCOLATE TYPE A POTATO; STARCH, CORN; STEARIC ACID

PredniSONE Tablets, USP 1 mg

DESCRIPTION

Glucocorticoids are adrenocortical steroids, both naturally occurring and synthetic, that are readily absorbed from the gastrointestinal tract. The formula for prednisone is C21H26O5. Chemically, it is 17,21-dihydroxypregna-1,4-diene-3,11,20-trione and has the following structure:

Prednisone is a white to practically white, odorless, crystalline powder and has a molecular weight of 358.43. It melts at about 230°C with some decomposition. Prednisone is very slightly soluble in water, slightly soluble in alcohol, chloroform, dioxane, and methanol. Prednisone Tablets, USP contain 1 mg Prednisone, USP.

The inactive ingredients for Prednisone Tablets, USP include: Microcrystalline Cellulose, Lactose Monohydrate, Pregelatinized Starch, Stearic Acid, Sodium Starch Glycolate and Magnesium Stearate.

ACTIONS

Naturally occurring glucocorticoids (hydrocortisone and cortisone), which also have salt-retaining properties, are used as replacement therapy in adrenocortical deficiency states. Their synthetic analogs, such as prednisone, are primarily used for their potent anti-inflammatory effects in disorders of many organ systems.

Glucocorticoids, such as prednisone, cause profound and varied metabolic effects. In addition, they modify the body's immune response to diverse stimuli.

INDICATIONS

Endocrine disorders: primary or secondary adrenocortical insufficiency (hydrocortisone or cortisone is the first choice; synthetic analogs may be used in conjunction with mineralocorticoids where applicable; in infancy mineralocorticoid supplementation is of particular importance), congenital adrenal hyperplasia, nonsuppurative thyroiditis, hypercalcemia associated with cancer.

Rheumatic disorders: as adjunctive therapy for short-term administration (to tide the patient over an acute episode or exacerbation) in: psoriatic arthritis; rheumatoid arthritis, including juvenile rheumatoid arthritis (selected cases may require low-dose maintenance therapy); ankylosing spondylitis; acute and subacute bursitis; acute nonspecific tenosynovitis; acute gouty arthritis; post-traumatic osteoarthritis; synovitis of osteoarthritis; epicondylitis.

Collagen diseases: during an exacerbation or as maintenance therapy in selected cases of: systemic lupus erythematosus, acute rheumatic carditis.

Dermatologic diseases: pemphigus, bullous dermatitis herpetiformis, severe erythema multiforme (Stevens-Johnson syndrome), exfoliative dermatitis, mycosis fungoides, severe psoriasis, severe seborrheic dermatitis.

Allergic states: control of severe or incapacitating allergic conditions intractable to adequate trials of conventional treatment: seasonal or perennial allergic rhinitis, serum sickness, bronchial asthma, contact dermatitis, atopic dermatitis, drug hypersensitivity reactions.

Ophthalmic diseases: severe acute and chronic allergic and inflammatory processes involving the eye and its adnexa, such as: allergic conjunctivitis, keratitis, allergic corneal marginal ulcers, herpes zoster ophthalmicus, iritis and iridocyclitis, chorioretinitis, anterior segment inflammation, diffuse posterior uveitis and choroiditis, optic neuritis, sympathetic ophthalmia.

Respiratory diseases: symptomatic sarcoidosis, Loeffler's syndrome not manageable by other means, berylliosis, fulminating or disseminated pulmonary tuberculosis when used concurrently with appropriate antituberculous chemotherapy, aspiration pneumonitis.

Hematologic disorders: idiopathic thrombocytopenic purpura in adults, secondary thrombocytopenia in adults, acquired (autoimmune) hemolytic anemia, erythroblastopenia (RBC anemia), congenital (erythroid) hypoplastic anemia.

Neoplastic diseases: for palliative management of: leukemias and lymphomas in adults, acute leukemia of childhood.

Edematous states: to induce a diuresis or remission of proteinuria in the nephrotic syndrome, without uremia, of the idiopathic type or that due to lupus erythematosus.

Gastrointestinal diseases: to tide the patient over a critical period of the disease in: ulcerative colitis, regional enteritis.

Miscellaneous: tuberculous meningitis with subarachnoid block or impending block when used concurrently with appropriate antituberculous chemotherapy, trichinosis with neurologic or myocardial involvement.

In addition to the above indications, Prednisone Tablets, USP are indicated for systemic dermatomyositis (polymyositis).

CONTRAINDICATIONS

Prednisone Tablets, USP are contraindicated in systemic fungal infections.

WARNINGS

In patients on corticosteroid therapy subjected to unusual stress, increased dosage of rapidly acting corticosteroids before, during, and after the stressful situation is indicated.

Corticosteroids may mask some signs of infection and new infections may appear during their use. There may be decreased resistance and inability to localize infection when corticosteroids are used.

Prolonged use of corticosteroids may produce posterior subcapsular cataracts, glaucoma with possible damage to the optic nerves, and may enhance the establishment of secondary ocular infections due to fungi or viruses.

Usage in pregnancy

Since adequate human reproduction studies have not been done with corticosteroids, the use of these drugs in pregnancy, nursing mothers or women of childbearing potential requires that the possible benefits of the drug be weighed against the potential hazards to the mother and embryo or fetus. Infants born of mothers who have received substantial doses of corticosteroids during pregnancy should be carefully observed for signs of hypoadrenalism.

Average and large doses of hydrocortisone or cortisone can cause elevation of blood pressure, salt and water retention, and increased excretion of potassium. These effects are less likely to occur with the synthetic derivatives except when used in large doses. Dietary salt restriction and potassium supplementation may be necessary. All corticosteroids increase calcium excretion.

While on corticosteroid therapy patients should not be vaccinated against smallpox. Other immunization procedures should not be undertaken in patients who are on corticosteroids, especially on high doses, because of possible hazards of neurological complications and a lack of antibody response.

Persons who are on drugs which suppress the immune system are more susceptible to infections than healthy individuals. Chickenpox and measles, for example, can have a more serious or even fatal course in non-immune children or adults on corticosteroids. In such children, or adults who have not had these diseases, particular care should be taken to avoid exposure. How the dose, route, and duration of corticosteroid administration affects the risk of developing a disseminated infection is not known. The contribution of the underlying disease and/or prior corticosteroid treatment to the risk is also not known. If exposed to chickenpox, prophylaxis with varicella-zoster immune globulin (VZIG) may be indicated. If exposed to measles, prophylaxis with pooled intramuscular immunoglobulin (IG) may be indicated. (See the respective package inserts for complete VZIG and IG prescribing information.) If chickenpox develops, treatment with antiviral agents may be considered.

The use of Prednisone Tablets, USP in active tuberculosis should be restricted to those cases of fulminating or disseminated tuberculosis in which the corticosteroid is used for the management of the disease in conjunction with an appropriate antituberculous regimen.

If corticosteroids are indicated in patients with latent tuberculosis or tuberculin reactivity, close observation is necessary as reactivation of the disease may occur. During prolonged corticosteroid therapy, these patients should receive chemoprophylaxis.

PRECAUTIONS

Information for Patients

Persons who are on immunosuppressant doses of corticosteroids should be warned to avoid exposure to chickenpox or measles. Patients should also be advised that if they are exposed, medical advice should be sought without delay.

General: Drug-induced, secondary adrenocortical insufficiency may be minimized by gradual reduction of dosage. This type of relative insufficiency may persist for months after discontinuation of therapy; therefore, in any situation of stress occurring during that period, hormone therapy should be reinstituted. Since mineralocorticoid secretion may be impaired, salt and/or a mineralocorticoid should be administered concurrently.

There is an enhanced effect of corticosteroids in patients with hypothyroidism and in those with cirrhosis.

Corticosteroids should be used cautiously in patients with ocular herpes simplex because of possible corneal perforation.

The lowest possible dose of corticosteroid should be used to control the condition under treatment, and when reduction in dosage is possible, the reduction should be gradual.

Psychic derangements may appear when corticosteroids are used, ranging from euphoria, insomnia, mood swings, personality changes, and severe depression to frank psychotic manifestations. Also, existing emotional instability or psychotic tendencies may be aggravated by corticosteroids.

Aspirin should be used cautiously in conjunction with corticosteroids in hypoprothrombinemia.

Steroids should be used with caution in: nonspecific ulcerative colitis, if there is a probability of impending perforation, abscess or other pyogenic infection; diverticulitis; fresh intestinal anastomoses; active or latent peptic ulcer; renal insufficiency; hypertension; osteoporosis; and myasthenia gravis.

Growth and development of infants and children on prolonged corticosteroid therapy should be carefully observed.

ADVERSE REACTIONS

Fluid and electrolyte disturbances: sodium retention, fluid retention, congestive heart failure in susceptible patients, potassium loss, hypokalemic alkalosis, hypertension.

Musculoskeletal: muscle weakness, steroid myopathy, loss of muscle mass, osteoporosis, vertebral compression fractures, aseptic necrosis of femoral and humeral heads, pathologic fracture of long bones.

Gastrointestinal: peptic ulcer with possible perforation and hemorrhage, pancreatitis, abdominal distention, ulcerative esophagitis.

Dermatologic: impaired wound healing, thin fragile skin, petechiae and ecchymoses, facial erythema, increased sweating, may suppress reactions to skin tests.
Neurological: convulsions, increased intracranial pressure with papilledema (pseudotumor cerebri) usually after treatment, vertigo, headache.

Endocrine: menstrual irregularities; development of cushingoid state; suppression of growth in children; secondary adrenocortical and pituitary unresponsiveness, particularly in times of stress, as in trauma, surgery or illness; decreased carbohydrate tolerance; manifestations of latent diabetes mellitus; increased requirements of insulin or oral hypoglycemic agents in diabetics.

Ophthalmic: posterior subcapsular cataracts, increased intraocular pressure, glaucoma, exophthalmos.

Metabolic: negative nitrogen balance due to protein catabolism.

DOSAGE AND ADMINISTRATION

Dosage of Prednisone Tablets, USP should be individualized according to the severity of the disease and the response of the patient. For infants and children, the recommended dosage should be governed by the same considerations rather than strict adherence to the ratio indicated by age or body weight.

Hormone therapy is an adjunct to, and not a replacement for, conventional therapy.

Dosage should be decreased or discontinued gradually when the drug has been administered for more than a few days.

The severity, prognosis, expected duration of the disease, and the reaction of the patient to medication are primary factors in determining dosage.

If a period of spontaneous remission occurs in a chronic condition, treatment should be discontinued.

Blood pressure, body weight, routine laboratory studies, including two-hour postprandial blood glucose and serum potassium, and a chest X-ray should be obtained at regular intervals during prolonged therapy. Upper GI X-rays are desirable in patients with known or suspected peptic ulcer disease.

The initial dosage of prednisone may vary from 5 mg to 60 mg per day, depending on the specific disease entity being treated. In situations of less severity lower doses will generally suffice, while in selected patients higher initial doses may be required. The initial dosage should be maintained or adjusted until a satisfactory response is noted. If after a reasonable period of time there is a lack of satisfactory clinical response, prednisone should be discontinued and the patient transferred to other appropriate therapy. IT SHOULD BE EMPHASIZED THAT DOSAGE REQUIREMENTS ARE VARIABLE AND MUST BE INDIVIDUALIZED ON THE BASIS OF THE DISEASE UNDER TREATMENT AND THE RESPONSE OF THE PATIENT. After a favorable response is noted, the proper maintenance dosage should be determined by decreasing the initial drug dosage in small decrements at appropriate time intervals until the lowest dosage which will maintain an adequate clinical response is reached. It should be kept in mind that constant monitoring is needed in regard to drug dosage. Included in the situations which may make dosage adjustments necessary are changes in clinical status secondary to remissions or exacerbations in the disease process, the patient's individual drug responsiveness, and the effect of patient exposure to stressful situations not directly related to the disease entity under treatment; in this latter situation it may be necessary to increase the dosage of prednisone for a period of time consistent with the patient's condition. If after long-term therapy the drug is to be stopped, it is recommended that it be withdrawn gradually rather than abruptly.

HOW SUPPLIED

1 mg (white, round, scored, imprinted PD4)

Bottles of 90 NDC 62135-470-90
Bottles of 180 NDC 62135-470-18

Store at 20°C to 25°C (68°F to 77°F) [See USP Controlled Room Temperature].
PROTECT FROM MOISTURE.

Dispense in a tight, child-resistant container as defined in the USP/NF.

Rx only

Manufactured by:
Tianjin Tianyao Pharmaceuticals Co., Ltd
Tianjin China 300457

Manufactured for:
Chartwell RX, LLC.

Congers, NY 10920

L71269

Revised 01/2023

PACKAGE LABEL-PRINCIPAL DISPLAY PANEL

Prednisone Tablets, USP 1 mg NDC 62135-470-90 - 90s Bottle Label

Prednisone Tablets, USP 1 mg NDC 62135-470-18 - 180s Bottle Label